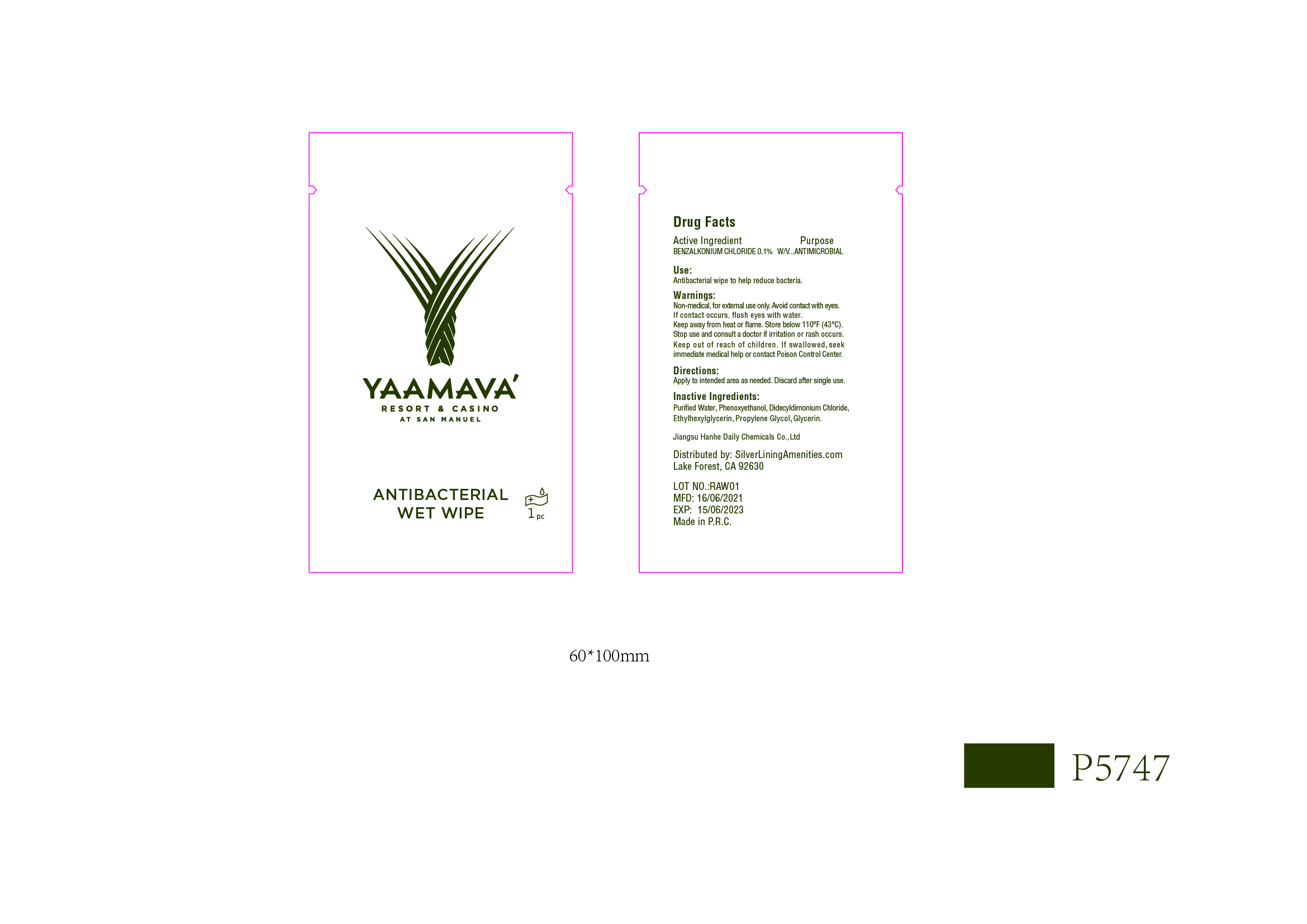 DRUG LABEL: YAAMAVA Antibacterial Wet Wipe
NDC: 73027-217 | Form: SOLUTION
Manufacturer: JIANGSU HANHE DAILY CHEMICALS CO., LTD.
Category: otc | Type: HUMAN OTC DRUG LABEL
Date: 20211102

ACTIVE INGREDIENTS: BENZALKONIUM CHLORIDE 0.1 g/100 mL
INACTIVE INGREDIENTS: GLYCERIN; ETHYLHEXYLGLYCERIN; WATER; PHENOXYETHANOL; PROPYLENE GLYCOL; DIDECYLDIMONIUM CHLORIDE

73027-217 Yaamava wipe

Active Ingredient

Benzalkonium Chloride 0.1% w/v

Purpose

Antimicrobial

Use

Antibacterial wipe to help reduce bacteria

Warnings

Non Medical. For external use only.

Avoid contact with eyes. If contact occurs, flush eyes with water

Keep away from heat or flame. Store below 110F (43C)

Stop use and consult a doctor if irritation or rash occurs.

Keep out of reach of children. If swallowed, seek immediate medical help or contact a Poison Control Center

Directions

- Apply to intended area as needed. Discard after single use

Inactive ingredients

Water, Phenoxyethanol, Didecyldimonium Chloride, Ethylhexylglycerin, Propylene Glycol, Glycerin